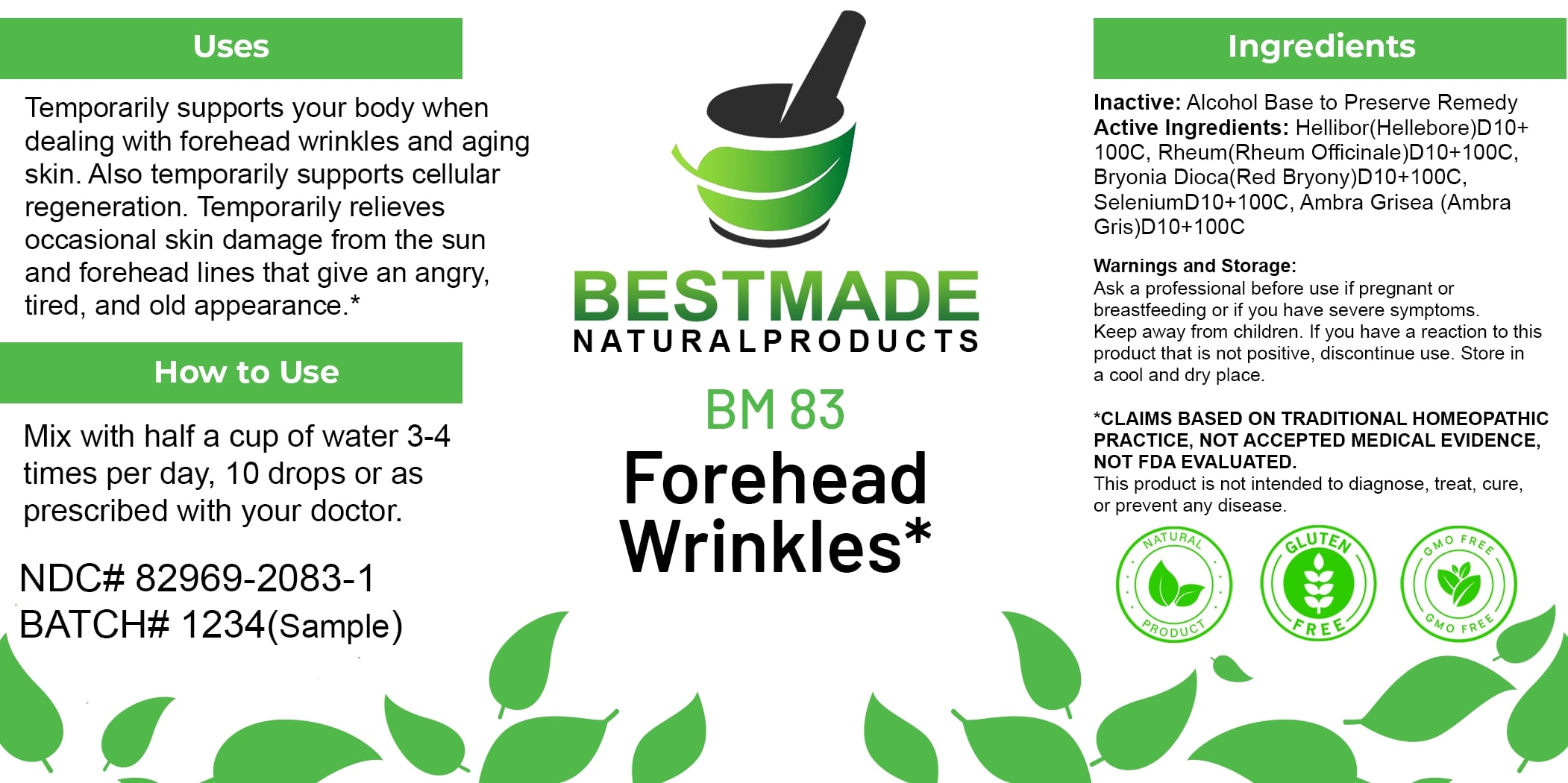 DRUG LABEL: Bestmade Natural Products BM83
NDC: 82969-2083 | Form: LIQUID
Manufacturer: Bestmade Natural Products
Category: homeopathic | Type: HUMAN OTC DRUG LABEL
Date: 20250131

ACTIVE INGREDIENTS: BRYONIA DIOICA ROOT 100 [hp_C]/100 [hp_C]; AMBERGRIS 100 [hp_C]/100 [hp_C]; SELENIUM 100 [hp_C]/100 [hp_C]; RHEUM OFFICINALE ROOT 100 [hp_C]/100 [hp_C]; HELLEBORUS NIGER ROOT 100 [hp_C]/100 [hp_C]
INACTIVE INGREDIENTS: ALCOHOL 100 [hp_C]/100 [hp_C]

BM83

DOSAGE AND ADMINISTRATION

How to Use

Mix with half a cup of water 3-4 times per day, 10 drops or as prescribed with your doctor.

INACTIVE INGREDIENT

Ingredients

Inactive: Alcohol Base to Preserve Remedy

ACTIVE INGREDIENT

Active Ingredients: Hellibor(Hellebore)D10+100C, Rheum(Rheum Officinale)D10+100C, Bryonia Dioca(Red Bryony)D10+100C, SeleniumD10+100C, Ambra Grisea (Ambra Gris)D10+100C

Uses

Temporarily supports your body when dealing with forehead wrinkles and aging skin. Also temporarily supports cellular regeneration. Temporarily relieves occasional skin damage from the sun and forehead lines that give an angry, tired, and old appearance.*

*CLAIMS BASED ON TRADITIONAL HOMEOPATHIC PRACTICE, NOT ACCEPTED MEDICAL EVIDENCE, NOT FDA EVALUATED.

This product is not intended to diagnose, treat, cure, or prevent any disease.

Uses

Temporarily supports your body when dealing with forehead wrinkles and aging skin. Also temporarily supports cellular regeneration. Temporarily relieves occasional skin damage from the sun and forehead lines that give an angry, tired, and old appearance.*

*CLAIMS BASED ON TRADITIONAL HOMEOPATHIC PRACTICE, NOT ACCEPTED MEDICAL EVIDENCE, NOT FDA EVALUATED.

This product is not intended to diagnose, treat, cure, or prevent any disease.

KEEP OUT OF REACH OF CHILDREN

Warnings and Storage:

Ask a professional before use if pregnant or breastfeeding or if you have severe symptoms. Keep away from children. If you have a reaction to this product that is not positive, discontinue use. Store in a cool and dry place.

Warnings and Storage:

Ask a professional before use if pregnant or breastfeeding or if you have severe symptoms. Keep away from children. If you have a reaction to this product that is not positive, discontinue use. Store in a cool and dry place.

*CLAIMS BASED ON TRADITIONAL HOMEOPATHIC PRACTICE, NOT ACCEPTED MEDICAL EVIDENCE, NOT FDA EVALUATED.

This product is not intended to diagnose, treat, cure, or prevent any disease.

Entire package label